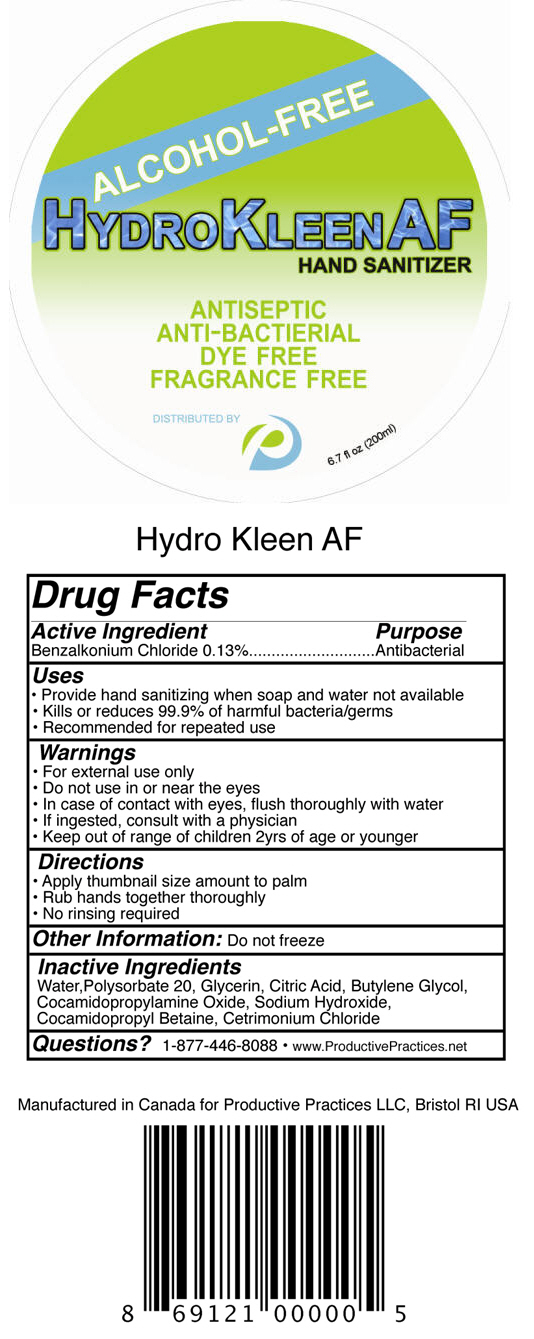 DRUG LABEL: Hydro Kleen AF
NDC: 69129-010 | Form: LIQUID
Manufacturer: Productive Practices
Category: otc | Type: HUMAN OTC DRUG LABEL
Date: 20140801

ACTIVE INGREDIENTS: Benzalkonium Chloride 0.13 g/1 mL
INACTIVE INGREDIENTS: Water; Polysorbate 20; Glycerin; Citric Acid Monohydrate; Butylene Glycol; Cocamidopropylamine Oxide; Sodium Hydroxide; Cocamidopropyl Betaine; CETRIMONIUM CHLORIDE

Hydro Kleen AF

Drug Facts

Active Ingredient

Benzalkonium Chloride 0.13%

Purpose

Antibacterial

Uses

- Provide hand sanitizing when soap and water not available
- Kills or reduces 99.9% of harmful bacteria/germs
- Recommended for repeated use

Warnings

- For external use only

- Do not use in or near the eyes

WHEN USING

- In case of contact with eyes, flush thoroughly with water

ASK DOCTOR

- If ingested, consult with a physician

KEEP OUT OF REACH OF CHILDREN

- Keep out of range of children 2yrs of age or younger

Directions

- Apply thumbnail size amount to palm
- Rub hands together thoroughly
- No rinsing required

Other Information

Do not freeze

Inactive Ingredients

Water, Polysorbate 20, Glycerin, Citric Acid, Butylene Glycol, Cocamidopropylamine Oxide, Sodium Hydroxide, Cocamidopropyl Betaine, Cetrimonium Chloride

Questions?

1-877-446-8088 • www.ProductivePractices.net

PRINCIPAL DISPLAY PANEL - 200 mL Bottle Label

ALCOHOL-FREE

HYDROKLEENAF
HAND SANITIZER

ANTISEPTIC
ANTI-BACTIERIAL
DYE FREE
FRAGRANCE FREE

DISTRIBUTED BY

6.7 fl oz (200ml)